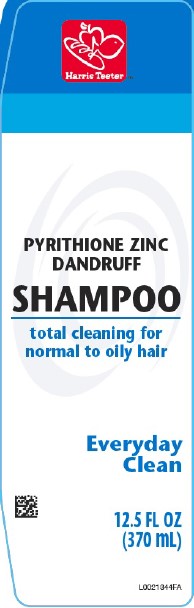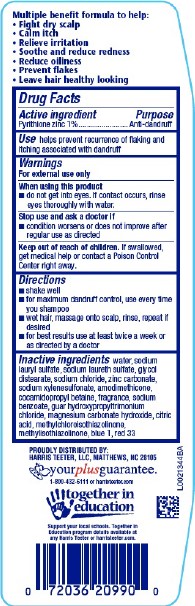 DRUG LABEL: Everyday Clean Dandruff
NDC: 72036-153 | Form: SHAMPOO
Manufacturer: Harris Teeter
Category: otc | Type: HUMAN OTC DRUG LABEL
Date: 20260204

ACTIVE INGREDIENTS: PYRITHIONE ZINC 10 mg/1 mL
INACTIVE INGREDIENTS: WATER; SODIUM LAURYL SULFATE; SODIUM LAURETH SULFATE; GLYCOL DISTEARATE; SODIUM CHLORIDE; ZINC CARBONATE; SODIUM XYLENESULFONATE; AMODIMETHICONE (800 CST); COCAMIDOPROPYL BETAINE; SODIUM BENZOATE; GUAR HYDROXYPROPYLTRIMONIUM CHLORIDE (1.7 SUBSTITUENTS PER SACCHARIDE); MAGNESIUM CARBONATE HYDROXIDE; CITRIC ACID MONOHYDRATE; METHYLCHLOROISOTHIAZOLINONE; METHYLISOTHIAZOLINONE; FD&C BLUE NO. 1; D&C RED NO. 33

Harris Teeter 153.008/153AZ rev1-BD
Everyday Clean Dandruff Shampoo

Claims

Multiple benefit formula to help:

- Fight dry scalp
- Calm Itch
- Relieve Irritation
- Soothe and reduce redness
- Reduce oiliness
- Prevent flakes
- Leave hair healthy looking

Active ingredient

Pyrithione zinc 1%

Purpose

Anti-dandruff

Use

helps prevent recurrence of flaking and itching associated with dandruff

Warnings

For external use only

When using this product

- do not get into eyes. If contact occurs, rinse eyes thoroughly with water.

Stop use and ask a doctor if

- condition worsens or does not improve after regular use as directed

Keep out of reach of children.

If swallowed, get medical help or contact a Poison Control Center right away.

Directions

- shake well
- for maximum dandruff control, use every time you shampoo
- wet hair massage onto scalp, rinse, repeat if desired
- for best results use at least twice a week or as directed by a doctor

inactrive ingredients

water, sodium lauryl sulfate, sodium laureth sulfate, glycol distearate, sodium chloride, zinc carbonate, sodium xylenesulfonate, amodimethicone, cocamidopropyl betaine, fragrance, sodium benzoate, guar hydroxypropyltrimonium chloride, magnesium carbonate hydroxide, citric acid, methylchloroisothiazolinone, methylisothiazolinone, blue 1, red 33

Adverse reaction

PROUDLY DISTRIBUTED BY:

HARRIS TEETER, LLC, MATTHEWS, NC 28105

your plus guarantee

1-800-432-6111 or harristeeter.com

together in eduction

Suppor your local schools. Together in Education program details available at any Harris Teeter or harristetter.com.

Principal display panel

Harris Teeter™

PYRITHIONE ZINC

DANDRUFF

SHAMPOO

total cleaning for normal to oil hair

Everyday Clean

12.5 FL OZ (370 mL)